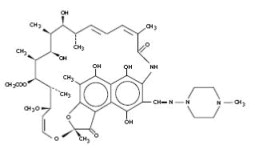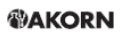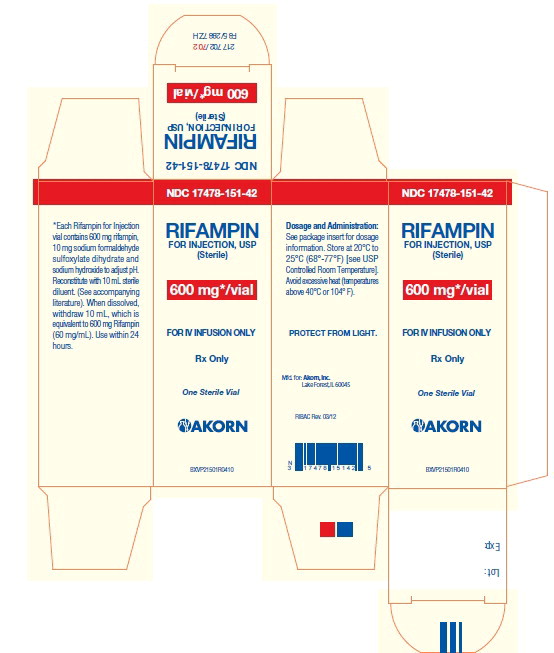 DRUG LABEL: Rifampin
NDC: 17478-151 | Form: INJECTION, POWDER, LYOPHILIZED, FOR SOLUTION
Manufacturer: Akorn
Category: prescription | Type: HUMAN PRESCRIPTION DRUG LABEL
Date: 20220913

ACTIVE INGREDIENTS: RIFAMPIN 600 mg/10 mL
INACTIVE INGREDIENTS: SODIUM FORMALDEHYDE SULFOXYLATE DIHYDRATE 10 mg/10 mL; SODIUM HYDROXIDE

RIFAMPIN FOR INJECTION USP

Rx ONLY

To reduce the development of drug-resistant bacteria and maintain the effectiveness of rifampin for injection USP and other antibacterial drugs, rifampin should be used only to treat or prevent infections that are proven or strongly suspected to be caused by bacteria.

DESCRIPTION

Rifampin for injection USP contains rifampin 600 mg, sodium formaldehyde sulfoxylate dihydrate 10 mg, and sodium hydroxide to adjust pH. Rifampin for injection is a sterile, lyophilized powder for intravenous infusion only.

Rifampin is a semisynthetic antibiotic derivative of rifamycin SV. Rifampin is a red-brown crystalline powder very slightly soluble in water at neutral pH, freely soluble in chloroform, soluble in ethyl acetate and in methanol. Its molecular weight is 822.95 and its chemical formula is C43H58N4O12. The chemical name for rifampin is either:

3-[[(4-Methyl-1-piperazinyl)imino]methyl]rifamycin

or

5,6,9,17,19,21-hexahydroxy-23-methoxy-2,4,12,16,20,22–heptamethyl-8-[N-(4-methyl-1-piperazinyl)formimidoyl]-2,7- (epoxypentadeca[1,11,13]trienimino)naphtho[2,1-b]furan-1,11(2H)-dione 21-acetate.

Its structural formula is:

CLINICAL PHARMACOLOGY

Intravenous Administration

After intravenous administration of a 300 or 600 mg dose of rifampin infused over 30 minutes to healthy male volunteers (n=12), mean peak plasma concentrations were 9.0 ± 3.0 and 17.5 ± 5.0 mcg/mL, respectively. Total body clearances after the 300 and 600 mg IV doses were 0.19 ± 0.06 and 0.14 ± 0.03 L/hr/kg, respectively. Volumes of distribution at steady state were 0.66 ± 0.14 and 0.64 ± 0.11 L/kg for the 300 and 600 mg IV doses, respectively. After intravenous administration of 300 or 600 mg doses, rifampin plasma concentrations in these volunteers remained detectable for 8 and 12 hours, respectively (see Table).

Plasma Concentrations (mean ± standard deviation, mcg/mL)

Rifampin Dosage IV | 30 min | 1 hr | 2 hr | 4 hr | 8 hr | 12 hr
300 mg | 8.9±2.9 | 4.9±1.3 | 4.0±1.3 | 2.5±1.0 | 1.1±0.6 | <0.4
600 mg | 17.4±5.1 | 11.7±2.8 | 9.4±2.3 | 6.4±1.7 | 3.5±1.4 | 1.2±0.6

Plasma concentrations after the 600 mg dose, which were disproportionately higher (up to 30% greater than expected) than those found after the 300 mg dose, indicated that the elimination of larger doses was not as rapid.

After repeated once-a-day infusions (3 hr duration) of 600 mg in patients (n=5) for 7 days, concentrations of IV rifampin decreased from 5.81 ± 3.38 mcg/mL 8 hours after the infusion on day 1 to 2.6 ± 1.88 mcg/mL 8 hours after the infusion on day 7.

Rifampin is widely distributed throughout the body. It is present in effective concentrations in many organs and body fluids, including cerebrospinal fluid. Rifampin is about 80% protein bound. Most of the unbound fraction is not ionized and therefore diffuses freely into tissues.

Rifampin is rapidly eliminated in the bile and undergoes progressive enterohepatic circulation and deacetylation to the primary metabolite, 25-desacetyl-rifampin. This metabolite is microbiologically active. Less than 30% of the dose is excreted in the urine as rifampin or metabolites. Serum concentrations do not differ in patients with renal failure at a studied dose of 300 mg and consequently, no dosage adjustment is required.

Pediatrics

Intravenous Administration

In pediatric patients 0.25 to 12.8 years old (n=12), the mean peak serum concentration of rifampin at the end of a 30 minute infusion of approximately 300 mg/m^2 was 25.9 ± 1.3 mcg/mL; individual peak concentrations 1 to 4 days after initiation of therapy ranged from 11.7 to 41.5 mcg/mL; individual peak concentrations 5 to 14 days after initiation of therapy were 13.6 to 37.4 mcg/mL. The individual serum half-life of rifampin changed from 1.04 to 3.81 hours early in therapy to 1.17 to 3.19 hours 5 to 14 days after therapy was initiated.

Microbiology

Mechanism of Action

Rifampin inhibits DNA-dependent RNA polymerase activity in susceptible Mycobacterium tuberculosis organisms. Specifically, it interacts with bacterial RNA polymerase but does not inhibit the mammalian enzyme.

Resistance

Organisms resistant to rifampin are likely to be resistant to other rifamycins. In addition, resistance to rifampin has been determined to occur as single-step mutations of the DNA-dependent RNA polymerase. Since resistance can emerge rapidly, appropriate susceptibility tests should be performed in the event of persistent positive cultures.

Activity in vitro and in vivo

Rifampin has bactericidal activity in vitro against slow and intermittently growing M tuberculosis organisms.

Rifampin has been shown to be active against most strains of the following microorganisms, both in vitro and in clinical infections as described in the INDICATIONS AND USAGE section.

Aerobic Gram-Negative Microorganisms:
Neisseria meningitidis

"Other" Microorganisms:
Mycobacterium tuberculosis

The following in vitro data are available, but their clinical significance is unknown.

Rifampin exhibits in vitro activity against most strains of the following microorganisms; however, the safety and effectiveness of rifampin in treating clinical infections due to these microorganisms have not been established in adequate and well-controlled trials.

Aerobic Gram-Positive Microorganisms:
Staphylococcus aureus (including Methicillin-Resistant S. aureus/MRSA)
Staphylococcus epidermidis

Aerobic Gram-Negative Microorganisms:
Haemophilus influenzae

"Other" Microorganisms:
Mycobacterium leprae

β-lactamase production should have no effect on rifampin activity.

Susceptibility Testing

For specific information regarding susceptibility test criteria and associated test methods and quality control standards recognized by FDA for this drug, please see: www.fda.gov/STIC.

INDICATIONS AND USAGE

In the treatment of both tuberculosis and the meningococcal carrier state, the small number of resistant cells present within large populations of susceptible cells can rapidly become the predominant type. Bacteriologic cultures should be obtained before the start of therapy to confirm the susceptibility of the organism to rifampin and they should be repeated throughout therapy to monitor the response to treatment. Since resistance can emerge rapidly, susceptibility tests should be performed in the event of persistent positive cultures during the course of treatment. If test results show resistance to rifampin and the patient is not responding to therapy, the drug regimen should be modified.

Tuberculosis

Rifampin is indicated in the treatment of all forms of tuberculosis.

A three-drug regimen consisting of rifampin, isoniazid, and pyrazinamide [e.g., RIFATER®]^1 is recommended in the initial phase of short-course therapy which is usually continued for 2 months. The Advisory Council for the Elimination of Tuberculosis, the American Thoracic Society, and Centers for Disease Control and Prevention recommend that either streptomycin or ethambutol be added as a fourth drug in a regimen containing isoniazid (INH), rifampin, and pyrazinamide for initial treatment of tuberculosis unless the likelihood of INH resistance is very low. The need for a fourth drug should be reassessed when the results of susceptibility testing are known. If community rates of INH resistance are currently less than 4%, an initial treatment regimen with less than four drugs may be considered.

Following the initial phase, treatment should be continued with rifampin and isoniazid [eg, RIFAMATE®]^2 for at least 4 months. Treatment should be continued for longer if the patient is still sputum or culture positive, if resistant organisms are present, or if the patient is HIV positive.

Rifampin for injection is indicated for the initial treatment and retreatment of tuberculosis when the drug cannot be taken by mouth.

Meningococcal Carriers

Rifampin is indicated for the treatment of asymptomatic carriers of Neisseria meningitidis to eliminate meningococci from the nasopharynx. Rifampin is not indicated for the treatment of meningococcal infection because of the possibility of the rapid emergence of resistant organisms. (See WARNINGS).

Rifampin should not be used indiscriminately, and therefore, diagnostic laboratory procedures, including serotyping and susceptibility testing, should be performed for establishment of the carrier state and the correct treatment. So that the usefulness of rifampin in the treatment of asymptomatic meningococcal carriers is preserved, the drug should be used only when the risk of meningococcal disease is high.

To reduce the development of drug-resistant bacteria and maintain the effectiveness of rifampin and other antibacterial drugs, rifampin should be used only to treat or prevent infections that are proven or strongly suspected to be caused by susceptible bacteria. When culture and susceptibility information are available, they should be considered in selecting or modifying antibacterial therapy. In the absence of such data, local epidemiology and susceptibility patterns may contribute to the empiric selection of therapy.

CONTRAINDICATIONS

Rifampin for injection is contraindicated in patients with a history of hypersensitivity to rifampin or any of the components, or to any of the rifamycins. (See WARNINGS).

Rifampin is contraindicated in patients who are also receiving ritonavir-boosted saquinavir due to an increased risk of severe hepatocellular toxicity. (See PRECAUTIONS, Drug Interactions.)

Rifampin is contraindicated in patients who are also receiving atazanavir, darunavir, fosamprenavir, saquinavir, or tipranavir due to the potential of rifampin to substantially decrease plasma concentrations of these antiviral drugs, which may result in loss of antiviral efficacy and/or development of viral resistance.

WARNINGS

Rifampin has been shown to produce liver dysfunction. Fatalities associated with jaundice have occurred in patients with liver disease and in patients taking rifampin with other hepatotoxic agents. Patients with impaired liver function should be given rifampin only in cases of necessity and then with caution and under strict medical supervision. In these patients, careful monitoring of liver function, especially SGPT/ALT and SGOT/AST should be carried out prior to therapy and then every 2 to 4 weeks during therapy. If signs of hepatocellular damage occur, rifampin should be withdrawn.

In some cases, hyperbilirubinemia resulting from competition between rifampin and bilirubin for excretory pathways of the liver at the cell level can occur in the early days of treatment. An isolated report showing a moderate rise in bilirubin and/or transaminase level is not in itself an indication for interrupting treatment; rather, the decision should be made after repeating the tests, noting trends in the levels, and considering them in conjunction with the patient's clinical condition.

Rifampin has enzyme-inducing properties, including induction of delta amino levulinic acid synthetase. Isolated reports have associated porphyria exacerbation with rifampin administration.

The possibility of rapid emergence of resistant meningococci restricts the use of rifampin for injection to short-term treatment of the asymptomatic carrier state. Rifampin for injection is not to be used for the treatment of meningococcal disease.

Systemic hypersensitivity reactions, including Drug Reaction with Eosinophilia and Systemic Symptoms (DRESS) syndrome, may occur in patients receiving rifampin for injection (see ADVERSE REACTIONS). Signs and symptoms of hypersensitivity reactions may include fever, rash, urticaria, angioedema, hypotension, acute bronchospasm, conjunctivitis, thrombocytopenia, neutropenia, elevated liver transaminases or flu-like syndrome (weakness, fatigue, muscle pain, nausea, vomiting, headache, chills, aches, itching, sweats, dizziness, shortness of breath, chest pain, cough, syncope, palpitations). These reactions may be severe and DRESS may be fatal. Manifestations of hypersensitivity, such as fever, lymphadenopathy or laboratory abnormalities (including eosinophilia, liver abnormalities) may be present even though rash is not evident. Monitor patients receiving rifampin for injection for signs and/or symptoms of hypersensitivity reactions. If these signs or symptoms occur, discontinue rifampin for injection and administer supportive measures.

PRECAUTIONS

General

Rifampin for injection should be used with caution in patients with a history of diabetes mellitus, as diabetes management may be more difficult.

Prescribing rifampin in the absence of a proven or strongly suspected bacterial infection or a prophylactic indication is unlikely to provide benefit to the patient and increases the risk of the development of drug-resistant bacteria.

For the treatment of tuberculosis, rifampin is usually administered on a daily basis. Doses of rifampin greater than 600 mg given once or twice weekly have resulted in a higher incidence of adverse reactions, including the "flu syndrome" (fever, chills and malaise), hematopoietic reactions (leukopenia, thrombocytopenia, or acute hemolytic anemia), cutaneous, gastrointestinal, and hepatic reactions, shortness of breath, shock, anaphylaxis, and renal failure. Recent studies indicate that regimens using twice-weekly doses of rifampin 600 mg plus isoniazid 15 mg/kg are much better tolerated.

Rifampin is not recommended for intermittent therapy; the patient should be cautioned against intentional or accidental interruption of the daily dosage regimen since rare renal hypersensitivity reactions have been reported when therapy was resumed in such cases.

Rifampin has enzyme induction properties that can enhance the metabolism of endogenous substrates including adrenal hormones, thyroid hormones, and vitamin D. Rifampin and isoniazid have been reported to alter vitamin D metabolism. In some cases, reduced levels of circulating 25-hydroxy vitamin D and 1,25-dihydroxy vitamin D have been accompanied by reduced serum calcium and phosphate, and elevated parathyroid hormone.

Rifampin IV

For intravenous infusion only. Must not be administered by intramuscular or subcutaneous route. Avoid extravasation during injection: local irritation and inflammation due to extravascular infiltration of the infusion have been observed. If these occur, the infusion should be discontinued and restarted at another site.

Information for Patients

Patients should be counseled that antibacterial drugs including rifampin should only be used to treat bacterial infections. They do not treat viral infections (e.g., the common cold). When rifampin is prescribed to treat a bacterial infection, patients should be told that although it is common to feel better early in the course of therapy, the medication should be taken exactly as directed. Skipping doses or not completing the full course of therapy may (1) decrease the effectiveness of the immediate treatment and (2) increase the likelihood that bacteria will develop resistance and will not be treatable by rifampin or other antibacterial drugs in the future.

The patient should be told that rifampin may produce a discoloration (yellow, orange, red, brown) of the teeth, urine, sweat, sputum, and tears, and the patient should be forewarned of this. Soft contact lenses may be permanently stained.

The patient should be advised that the reliability of oral or other systemic hormonal contraceptives may be affected; consideration should be given to using alternative contraceptive measures.

Patients should be instructed to notify their physicians promptly if they experience any of the following: fever, loss of appetite, malaise, nausea and vomiting, darkened urine, yellowish discoloration of the skin and eyes, and pain or swelling of the joints.

Compliance with the full course of therapy must be emphasized, and the importance of not missing any doses must be stressed.

Laboratory Tests

Adults treated for tuberculosis with rifampin should have baseline measurements of hepatic enzymes, bilirubin, serum creatinine, a complete blood count, and a platelet count (or estimate). Baseline tests are unnecessary in pediatric patients unless a complicating condition is known or clinically suspected.

Patients should be seen at least monthly during therapy and should be specifically questioned concerning symptoms associated with adverse reactions. All patients with abnormalities should have follow-up, including laboratory testing, if necessary. Routine laboratory monitoring for toxicity in people with normal baseline measurements is generally not necessary.

Drug Interactions

Healthy subjects who received rifampin 600 mg once daily concomitantly with saquinavir 1000 mg/ritonavir 100 mg twice daily (ritonavir-boosted saquinavir) developed severe hepatocellular toxicity. Therefore, concomitant use of these medications is contraindicated. (See CONTRAINDICATIONS.)

Enzyme Induction: Rifampin is known to induce certain cytochrome P-450 enzymes. Administration of rifampin with drugs that undergo biotransformation through these metabolic pathways may accelerate elimination of coadministered drugs. To maintain optimum therapeutic blood levels, dosages of drugs metabolized by these enzymes may require adjustment when starting or stopping concomitantly administered rifampin.

Rifampin has been reported to substantially decrease the plasma concentrations of the following antiviral drugs: atazanavir, darunavir, fosamprenavir, saquinavir, and tipranavir. These antiviral drugs must not be co-administered with rifampin. (See CONTRAINDICATIONS.)

Rifampin has been reported to accelerate the metabolism of the following drugs: anticonvulsants (e.g., phenytoin), digitoxin, antiarrhythmics (e.g., disopyramide, mexiletine, quinidine, tocainide), oral anticoagulants, antifungals (e.g., fluconazole, itraconazole, ketoconazole), barbiturates, beta-blockers, calcium channel blockers (e.g., diltiazem, nifedipine, verapamil), chloramphenicol, clarithromycin, corticosteroids, cyclosporine, cardiac glycoside preparations, clofibrate, oral or other systemic hormonal contraceptives, dapsone, diazepam, doxycycline, fluoroquinolones (e.g., ciprofloxacin), haloperidol, oral hypoglycemic agents (sulfonylureas), levothyroxine, methadone, narcotic analgesics, progestins, quinine, tacrolimus, theophylline, tricyclic antidepressants (e.g., amitriptyline, nortriptyline) and zidovudine. It may be necessary to adjust the dosages of these drugs if they are given concurrently with rifampin.

Patients using oral or other systemic hormonal contraceptives should be advised to change to nonhormonal methods of birth control during rifampin therapy.

Rifampin has been observed to increase the requirements for anticoagulant drugs of the coumarin type. In patients receiving anticoagulants and rifampin concurrently, it is recommended that the prothrombin time be performed daily or as frequently as necessary to establish and maintain the required dose of anticoagulant.

Other Interactions: When the two drugs were taken concomitantly, decreased concentrations of atovaquone and increased concentrations of rifampin were observed.

Concurrent use of ketoconazole and rifampin has resulted in decreased serum concentrations of both drugs. Concurrent use of rifampin and enalapril has resulted in decreased concentrations of enalaprilat, the active metabolite of enalapril. Dosage adjustments should be made if indicated by the patient's clinical condition.

Concomitant antacid administration may reduce the absorption of rifampin. Daily doses of rifampin should be given at least 1 hour before the ingestion of antacids.

Probenecid and cotrimoxazole have been reported to increase the blood level of rifampin.

When rifampin is given concomitantly with either halothane or isoniazid, the potential for hepatotoxicity is increased. The concomitant use of rifampin and halothane should be avoided. Patients receiving both rifampin and isoniazid should be monitored close for hepatotoxicity.

Plasma concentrations of sulfapyridine may be reduced following the concomitant administration of sulfasalazine and rifampin. This finding may be the result of alteration in the colonic bacteria responsible for the reduction of sulfasalazine to sulfapyridine and mesalamine.

Drug/Laboratory Interactions

Cross-reactivity and false-positive urine screening tests for opiates have been reported in patients receiving rifampin when using the KIMS (Kinetic Interaction of Microparticles in Solution) method (e.g., Abuscreen OnLine opiates assay; Roche Diagnostic Systems). Confirmatory tests, such as gas chromatography/mass spectrometry, will distinguish rifampin from opiates.

Therapeutic levels of rifampin have been shown to inhibit standard microbiological assays for serum folate and vitamin B12. Thus, alternate assay methods should be considered. Transient abnormalities in liver function tests (e.g., elevation in serum bilirubin, alkaline phosphatase, and serum transaminases) and reduced biliary excretion of contrast media used for visualization of the gallbladder have also been observed. Therefore, these tests should be performed before the morning dose of rifampin.

Carcinogenesis, Mutagenesis, Impairment of Fertility

A few cases of accelerated growth of lung carcinoma have been reported in man, but a causal relationship with the drug has not been established. Hepatomas were increased in female (C3Hf/DP) mice dosed for 60 weeks with rifampicin followed by an observation period of 46 weeks, at 20 to 120 mg/kg (equivalent to 0.1 to 0.5 times the maximum dosage used clinically, based on body surface area comparisons). There was no evidence of tumorigenicity in male C3Hf/DP mice or in similar studies in BALB/c mice, or in two year studies in Wistar rats.

There was no evidence of mutagenicity in both prokaryotic (Salmonella typhi, Escherichia coli) and eukaryotic (Saccharomyces cerevisiae) bacteria, Drosophila melanogaster, or ICR/Ha Swiss mice. An increase in chromatid breaks was noted when whole blood cell cultures were treated with rifampin. Increased frequency of chromosomal aberrations was observed in vitro in lymphocytes obtained from patients treated with combinations of rifampin, isoniazid, and pyrazinamide and combinations of streptomycin, rifampin, isoniazid, and pyrazinamide.

Pregnancy –Teratogenic Effects

Category C. Rifampin has been shown to be teratogenic in rodents. Congenital malformations, primarily spina bifida were increased in the offspring of pregnant rats given rifampin during organogenesis at oral doses of 150 to 250 mg/kg/day (about 1 to 2 times the maximum recommended human dose based on body surface area comparisons). Cleft palate was increased in a dose-dependent fashion in fetuses of pregnant mice treated at oral doses of 50 to 200 mg/kg (about 0.2 to 0.8 times the maximum recommended human dose based on body surface area comparisons). Imperfect osteogenesis and embryotoxicity were also reported in pregnant rabbits given rifampin at oral doses up to 200 mg/kg/day (about 3 times the maximum recommended human dose based on body surface area comparisons). There are no adequate and well-controlled studies of rifampin in pregnant women. Rifampin has been reported to cross the placental barrier and appear in cord blood. Rifampin should be used during pregnancy only if the potential benefit justifies the potential risk to the fetus.

Pregnancy–Non-Teratogenic Effects

When administered during the last few weeks of pregnancy, rifampin can cause post-natal hemorrhages in the mother and infant for which treatment with vitamin K may be indicated.

Nursing Mothers

Because of the potential for tumorigenicity shown for rifampin in animal studies, a decision should be made whether to discontinue nursing or discontinue the drug, taking into account the importance of the drug to the mother.

Pediatric Use

See CLINICAL PHARMACOLOGY–Pediatrics; see also DOSAGE AND ADMINISTRATION.

Geriatric Use

Clinical studies of rifampin did not include sufficient numbers of subjects aged 65 and over to determine whether they respond differently from younger subjects. Other reported clinical experience has not identified differences in responses between the elderly and younger patients. Caution should therefore be observed in using rifampin in elderly patients. (See WARNINGS).

ADVERSE REACTIONS

Gastrointestinal

Heartburn, epigastric distress, anorexia, nausea, vomiting, jaundice, flatulence, cramps, and diarrhea have been noted in some patients. Although Clostridium difficile has been shown in vitro to be sensitive to rifampin, pseudomembranous colitis has been reported with the use of rifampin (and other broad spectrum antibiotics). Therefore, it is important to consider this diagnosis in patients who develop diarrhea in association with antibiotic use. Tooth discoloration (which may be permanent) may occur.

Hepatic

Transient abnormalities in liver function tests (e.g., elevations in serum bilirubin, alkaline phosphatase, serum transaminases) have been observed. Rarely, hepatitis or a shock-like syndrome with hepatic involvement and abnormal liver function tests has been reported.

Hematologic

Thrombocytopenia has occurred primarily with high dose intermittent therapy, but has also been noted after resumption of interrupted treatment. It rarely occurs during well supervised daily therapy. This effect is reversible if the drug is discontinued as soon as purpura occurs. Cerebral hemorrhage and fatalities have been reported when rifampin administration has been continued or resumed after the appearance of purpura.

Rare reports of disseminated intravascular coagulation have been observed.
Leukopenia, hemolytic anemia, and decreased hemoglobin have been observed.

Agranulocytosis has been reported very rarely.

Central Nervous System

Headache, fever, drowsiness, fatigue, ataxia, dizziness, inability to concentrate, mental confusion, behavioral changes, muscular weakness, pains in extremities, and generalized numbness have been observed.

Psychoses have been rarely reported.

Rare reports of myopathy have also been observed.

Ocular

Visual disturbances have been observed.

Endocrine

Menstrual disturbances have been observed.

Rare reports of adrenal insufficiency in patients with compromised adrenal function have been observed.

Renal

Elevations in BUN and serum uric acid have been reported. Rarely, hemolysis, hemoglobinuria, hematuria, interstitial nephritis, acute tubular necrosis, renal insufficiency, and acute renal failure have been noted. These are generally considered to be hypersensitivity reactions. They usually occur during intermittent therapy or when treatment is resumed following intentional or accidental interruption of a daily dosage regimen, and are reversible when rifampin is discontinued and appropriate therapy instituted.

Dermatologic

Cutaneous reactions are mild and self-limiting and do not appear to be hypersensitivity reactions. Typically, they consist of flushing and itching with or without a rash. More serious cutaneous reactions which may be due to hypersensitivity occur but are uncommon.

Hypersensitivity Reactions

Occasionally, pruritus, urticaria, rash, pemphigoid reaction, erythema multiforme including Stevens-Johnson Syndrome, toxic epidermal necrolysis, Drug Reaction with Eosinophilia and Systemic Symptoms syndrome (see WARNINGS), vasculitis, eosinophilia, sore mouth, sore tongue, and conjunctivitis have been observed.

Anaphylaxis has been reported rarely.

Miscellaneous

Edema of the face and extremities have been reported. Other reactions which have occurred with intermittent dosage regimens include "flu syndrome" (such as episodes of fever, chills, headache, dizziness, and bone pain), shortness of breath, wheezing, decrease in blood pressure and shock. The "flu syndrome" may also appear if rifampin is taken irregularly by the patient or if daily administration is resumed after a drug free interval.

To report SUSPECTED ADVERSE EVENTS, contact FDA at 1-800-FDA-1088 or www.fda.gov.

OVERDOSAGE

Signs and Symptoms

Nausea, vomiting, abdominal pain, pruritus, headache, and increasing lethargy will probably occur within a short time after ingestion; unconsciousness may occur when there is severe hepatic disease. Transient increases in liver enzymes and/or bilirubin may occur. Brownish-red or orange discoloration of the skin, urine, sweat, saliva, tears, and feces will occur, and its intensity is proportional to the amount ingested.

Liver enlargement, possibly with tenderness, can develop within a few hours after severe overdosage; bilirubin levels may increase and jaundice may develop rapidly. Hepatic involvement may be more marked in patients with prior impairment of hepatic function. Other physical findings remain essentially normal. A direct effect upon the hematopoietic system, electrolyte levels, or acid-base balance is unlikely.

Facial or periorbital edema has also been reported in pediatric patients. Hypotension, sinus tachycardia, ventricular arrhythmias, seizures and cardiac arrest were reported in some fatal cases.

Acute Toxicity

The minimum acute lethal or toxic dose is not well established. However, nonfatal acute overdoses in adults have been reported with doses ranging from 9 to 12 gm rifampin. Fatal acute overdoses in adults have been reported with doses ranging from 14 to 60 gm. Alcohol or a history of alcohol abuse was involved in some of the fatal and nonfatal reports. Nonfatal overdoses in pediatric patients ages 1 to 4 years old of 100 mg/kg for one to two doses has been reported.

Treatment

Intensive support measures should be instituted and individual symptoms treated as they arise. The airway should be secured and adequate respiratory exchange established. Since nausea and vomiting are likely to be present, gastric lavage within the first 2 to 3 hours after ingestion is probably preferable to induction of emesis. Following evacuation of the gastric contents, the instillation of activated charcoal slurry into the stomach may help absorb any remaining drug from the gastrointestinal tract. Antiemetic medication may be required to control severe nausea and vomiting.

Active diuresis (with measured intake and output) will help promote excretion of the drug. For severe cases, extracorporeal hemodialysis may be required. If this is not available, peritoneal dialysis can be used along with forced diuresis.

DOSAGE AND ADMINISTRATION

Rifampin for injection is administered by IV infusion (see INDICATIONS AND USAGE). IV doses are the same as those for oral.

See CLINICAL PHARMACOLOGY for dosing information in patients with renal failure.

Tuberculosis

Adults: 10 mg/kg, in a single daily administration, not to exceed 600 mg/day, IV.

Pediatric Patients: 10–20 mg/kg, not to exceed 600 mg/day, IV.

Rifampin is indicated in the treatment of all forms of tuberculosis. A three-drug regimen consisting of rifampin, isoniazid, and pyrazinamide [e.g., RIFATER®]^1 is recommended in the initial phase of short-course therapy which is usually continued for 2 months. The Advisory Council for the Elimination of Tuberculosis, the American Thoracic Society, and the Centers for Disease Control and Prevention recommend that either streptomycin or ethambutol be added as a fourth drug in a regimen containing isoniazid (INH), rifampin and pyrazinamide for initial treatment of tuberculosis unless the likelihood of INH resistance is very low. The need for a fourth drug should be reassessed when the results of susceptibility testing are known. If community rates of INH resistance are currently less than 4%, an initial treatment regimen with less than four drugs may be considered.

Following the initial phase, treatment should be continued with rifampin and isoniazid [e.g., RIFAMATE®]^2 for at least 4 months. Treatment should be continued for longer if the patient is still sputum or culture positive, if resistant organisms are present, or if the patient is HIV positive.

Preparation of Solution for IV Infusion: Reconstitute the lyophilized powder by transferring 10 mL of sterile water for injection to a vial containing 600 mg of rifampin for injection. Swirl vial gently to completely dissolve the antibiotic. The reconstituted solution contains 60 mg rifampin per mL and is stable at room temperature for 24 hours. Prior to administration, withdraw from the reconstituted solution a volume equivalent to the amount of rifampin calculated to be administered and add to 500 mL of infusion medium. Mix well and infuse at a rate allowing for complete infusion within 3 hours. Alternatively, the amount of rifampin calculated to be administered may be added to 100 mL of infusion medium and infused in 30 minutes.

Dilutions in dextrose 5% for injection (D5W) are stable at room temperature for up to 4 hours and should be prepared and used within this time. Precipitation of rifampin from the infusion solution may occur beyond this time. Dilutions in normal saline are stable at room temperature for up to 24 hours and should be prepared and used within this time. Other infusion solutions are not recommended.

Incompatibilities: Physical incompatibility (precipitate) was observed with undiluted (5 mg/mL) and diluted (1 mg/mL in normal saline) diltiazem hydrochloride and rifampin (6 mg/mL in normal saline) during simulated Y-site administration.

Meningococcal Carriers

Adults: For adults, it is recommended that 600 mg rifampin be administered twice daily for two days.

Pediatric Patients: Pediatric patients 1 month of age or older: 10 mg/kg (not to exceed 600 mg per dose) every 12 hours for two days.

Pediatric patients under 1 month of age: 5 mg/kg every 12 hours for two days.

HOW SUPPLIED

Rifampin for Injection USP, containing 600 mg of rifampin, is supplied in sterile glass vials, individually boxed (NDC # 17478-151-42).

Storage: Store at 25°C (77°F); excursions permitted to 15-30°C (59-86°F) [see USP Controlled Room Temperature]. Avoid excessive heat (temperatures above 40°C or 104°F). Protect from light.

REFERENCES

1. RIFATER® (rifampin, isoniazid, and pyrazinamide) is a registered trademark of Sanofi-Aventis U.S. LLC.
2. RIFAMATE® (rifampin and isoniazid) is a registered trademark of Sanofi-Aventis U.S. LLC.

Rx only

Manufactured for:
AKORN, Inc.
Lake Forest, IL 60045

RIBAN Rev. 11/18

257112

PRINCIPAL DISPLAY PANEL- 600 mg Vial Carton

NDC 17478-151-42

RIFAMPIN

FOR INJECTION, USP

(Sterile)

600 mg*/vial

FOR IV INFUSION ONLY

Rx Only

One Sterile Vial

AKORN